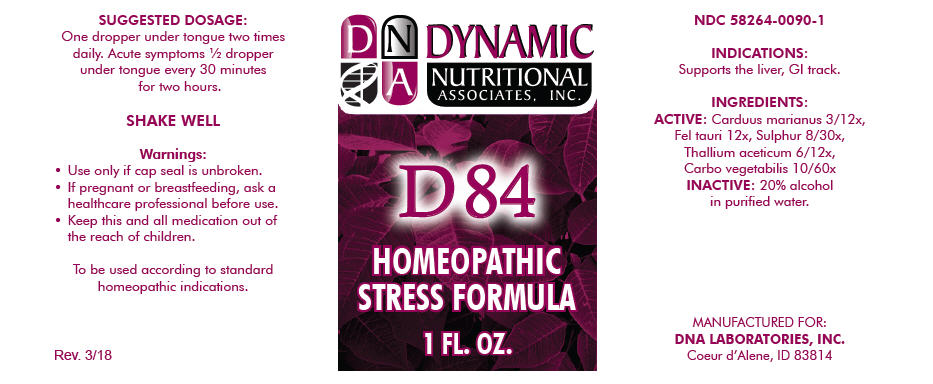 DRUG LABEL: D-84
NDC: 58264-0090 | Form: SOLUTION
Manufacturer: DNA Labs, Inc.
Category: homeopathic | Type: HUMAN OTC DRUG LABEL
Date: 20250113

ACTIVE INGREDIENTS: MILK THISTLE 3 [hp_X]/1 mL; BOS TAURUS BILE 12 [hp_X]/1 mL; SULFUR 8 [hp_X]/1 mL; THALLOUS ACETATE 6 [hp_X]/1 mL; ACTIVATED CHARCOAL 10 [hp_X]/1 mL
INACTIVE INGREDIENTS: ALCOHOL; WATER

D-84

NDC 58264-0090-1

INDICATIONS

PURPOSE

Supports the liver, GI track.

INGREDIENTS

ACTIVE

Carduus marianus 3/12x, Fel tauri 12x, Sulphur 8/30x, Thallium aceticum 6/12x, Carbo vegetabilis 10/60x

INACTIVE

20% alcohol in purified water.

SUGGESTED DOSAGE

One dropper under tongue two times daily. Acute symptoms ½ dropper under tongue every 30 minutes for two hours.

STORAGE AND HANDLING

SHAKE WELL

Warnings

- Use only if cap seal is unbroken.

PREGNANCY OR BREAST FEEDING

- If pregnant or breastfeeding, ask a healthcare professional before use.

KEEP OUT OF REACH OF CHILDREN

- Keep this and all medication out of the reach of children.

To be used according to standard homeopathic indications.

PRINCIPAL DISPLAY PANEL - 1 FL. OZ. Bottle Label

DYNAMIC
NUTRITIONAL
ASSOCIATES, INC.

D 84

HOMEOPATHIC
STRESS FORMULA

1 FL. OZ.